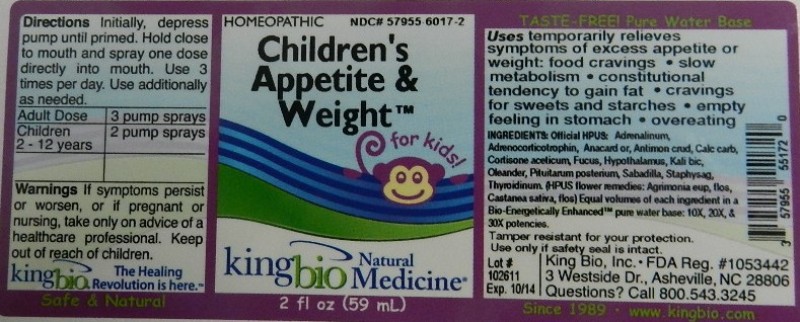 DRUG LABEL: Childrens Appetite Weight
NDC: 57955-6017 | Form: LIQUID
Manufacturer: King Bio Inc.
Category: homeopathic | Type: HUMAN OTC DRUG LABEL
Date: 20111222

ACTIVE INGREDIENTS: CORTICOTROPIN 10 [hp_X]/59 mL; EPINEPHRINE 10 [hp_X]/59 mL; SEMECARPUS ANACARDIUM JUICE 10 [hp_X]/59 mL; ANTIMONY TRISULFIDE 10 [hp_X]/59 mL; OYSTER SHELL CALCIUM CARBONATE, CRUDE 10 [hp_X]/59 mL; CORTISONE ACETATE 10 [hp_X]/59 mL; FUCUS VESICULOSUS 10 [hp_X]/59 mL; BOS TAURUS HYPOTHALAMUS 10 [hp_X]/59 mL; POTASSIUM DICHROMATE 10 [hp_X]/59 mL; NERIUM OLEANDER LEAF 10 [hp_X]/59 mL; SUS SCROFA PITUITARY GLAND 10 [hp_X]/59 mL; SCHOENOCAULON OFFICINALE SEED 10 [hp_X]/59 mL; DELPHINIUM STAPHISAGRIA SEED 10 [hp_X]/59 mL; THYROID, UNSPECIFIED 10 [hp_X]/59 mL; AGRIMONIA EUPATORIA FLOWER 10 [hp_X]/59 mL; CASTANEA SATIVA FLOWER 10 [hp_X]/59 mL
INACTIVE INGREDIENTS: WATER

Children's Appetite and weight

Active Ingredients

Official HPUS: Adrenocorticotrophin, Adrenalinum, Anacardium Orientale, Antimonium Crudum, Calcarea Carbonica, Cortisone Aceticum, Fucus Vesiculosus, Hypothalamus, Kali Bichromicum, Oleander, Pituitarum Posterium, Sabadilla, Staphysagria, Thyroidinum.

HPUS flower remedies: Agrimonia Eupatoria, Flos, Castanea Sativa, Flos.

Reference image children.jpg

Inactive Ingredient

Equal volumes of each ingredient in a Bio-Energetically Enhanced pure water base: 10X, 20X, and 30X potencies.

Reference image children.jpg

Dosage and Administration

Directions initially, depress pump until primed. Hold close to mouth and spray one dose directly into mouth. Use 3 times per day. Use additionally as needed.

Adult Dose 3 pump sprays

Children (2-12 years) 2 pump sprays

Reference image children.jpg

Purpose

Uses temporarily relieves symptoms of excess appetite or weight: food cravings, slow metabolism, constitutional tendency to gain fat, cravings for sweets and starches, empty feeling in stomach, overeating.

Reference image children.jpg

Warnings

If symptoms persist or worsen, or if pregnant or nursing, take only on advice of a healthcare professional.

Tamper resistant for your protection. Use only if safety seal is intact.

Reference image children.jpg

Keep out of reach of children.

Reference image children.jpg

Indications and Usage

Uses temporarily relieves symptoms of excess appetite or weight

- food cravings
- slow metabolism
- constitutional tendency to gain fat
- cravings for sweets and starches
- empty feeling in stomach
- overeating

Reference image children.jpg

PACKAGE LABEL

King Bio Inc.

3 Westside Drive

Asheville, NC 28806

www.kingbio.com

Questions? Call 800.543.3245